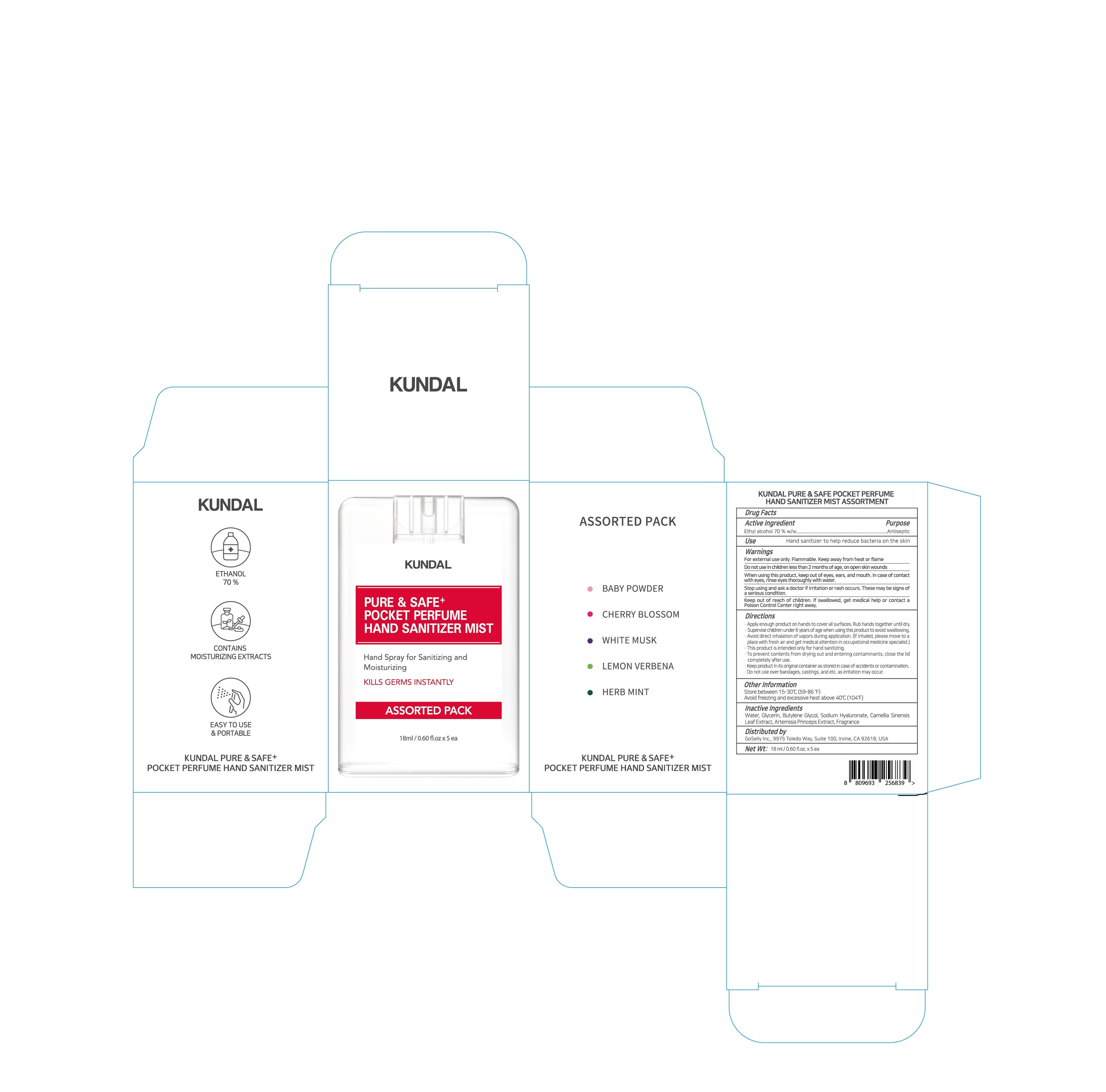 DRUG LABEL: KUNDAL PURE and SAFE POCKET PERFUME HAND SANITIZER MIST ASSORTMENT
NDC: 74773-0025 | Form: KIT | Route: TOPICAL
Manufacturer: THESKINFACTORY Co., Ltd.
Category: otc | Type: HUMAN OTC DRUG LABEL
Date: 20201004

ACTIVE INGREDIENTS: ALCOHOL 70 g/100 mL; ALCOHOL 70 g/100 mL; ALCOHOL 70 g/18 mL; ALCOHOL 70 g/100 mL; ALCOHOL 70 g/100 mL
INACTIVE INGREDIENTS: WATER; WATER; WATER; WATER; GLYCERIN; WATER

Drug Facts

ACTIVE INGREDIENT

niacinamide, adenosine

INACTIVE INGREDIENT

see attached product label

PURPOSE

see attached product label

keep out of reach of the children

indications are attached in product label

WARNINGS

Use it for your own use only.

For external use only.

Discontinue use if adverse reaction occurs.

Contact a physician if symptoms persist.

Store at room temperature

.Do not reuse it as a disposable product.

Please use it immediately after opening.

DOSAGE AND ADMINISTRATION

for topical use only